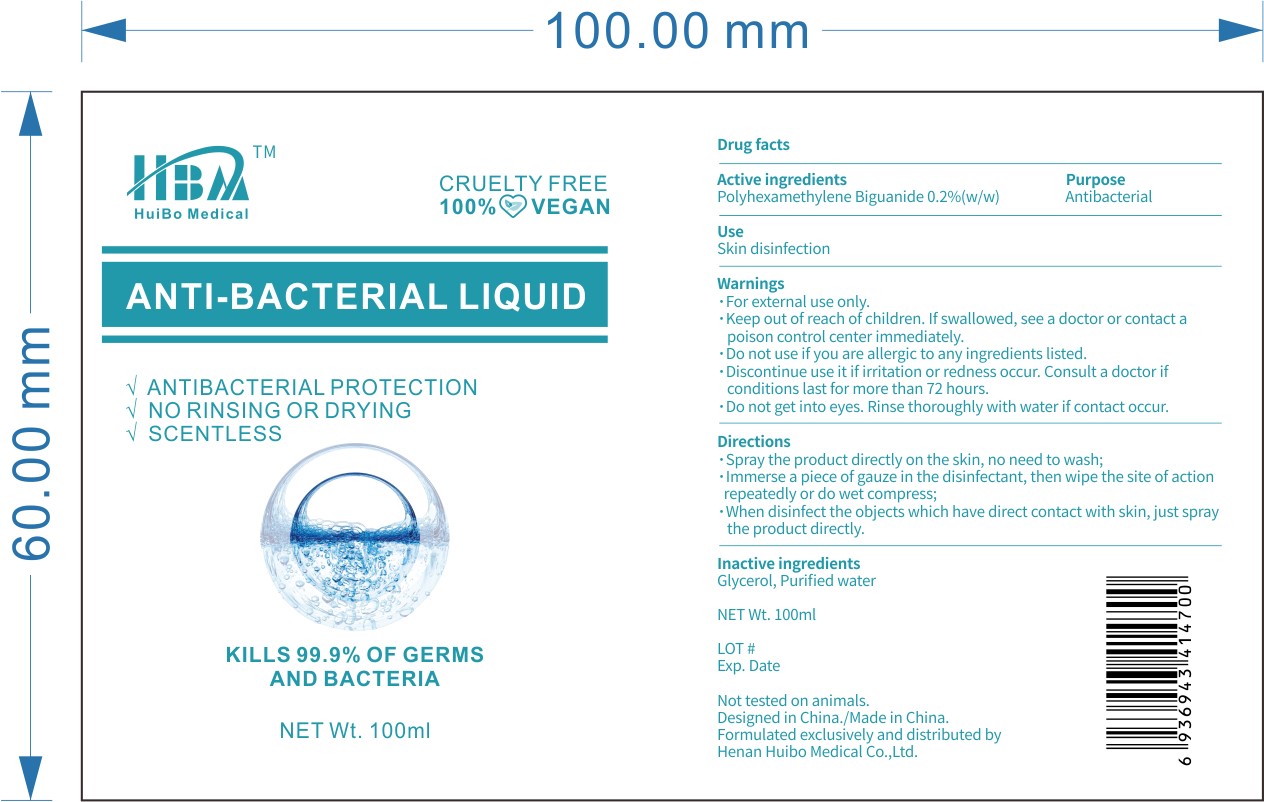 DRUG LABEL: HBA Anti bacterial Liquid
NDC: 79158-003 | Form: SPRAY
Manufacturer: Henan Huibo Medical Co., Ltd.
Category: otc | Type: HUMAN OTC DRUG LABEL
Date: 20200722

ACTIVE INGREDIENTS: POLIHEXANIDE 0.2 g/100 mL
INACTIVE INGREDIENTS: WATER; GLYCEROL FORMAL

POLIHEXANIDE Spray

Active Ingredient

Polyhexamethylene biguanide 0.2% w/w

Purpose

Antibacterial

Use

■ Skin disinfection

WARNINGS

For external use only

Do not use if you are allergic to any ingredients listed

Discontinue use if irritation or redness occur. Consult a doctor if condition lasts for more than 72 hours

Do not get into eyes. Rinse thoroughly with water if contact occurs

Keep out of reach of children. If swallowed, see a doctor or contact a poison control center immediately

Directions

Spray the product directly on the skin, no need to wash

Immerse a piece of gauze in the disinfectant, then wipe the site of action repeatedly or do wet compress

When disinfect the objects which have direct contact with skin, just spray the product directly

Inactive ingredients

Water, Glycerol